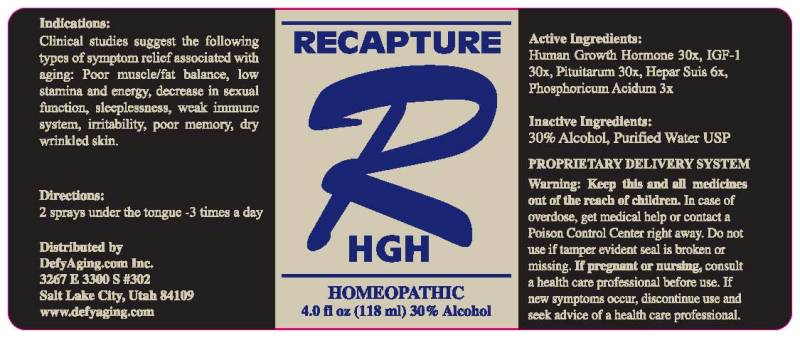 DRUG LABEL: Recapture
NDC: 45343-0001 | Form: SPRAY
Manufacturer: DefyAging.com Inc.
Category: homeopathic | Type: HUMAN OTC DRUG LABEL
Date: 20120629

ACTIVE INGREDIENTS: PHOSPHORIC ACID 3 [hp_X]/1 mL; PORK LIVER 6 [hp_X]/1 mL; SOMATROPIN 30 [hp_X]/1 mL; MECASERMIN 30 [hp_X]/1 mL; SUS SCROFA PITUITARY GLAND 30 [hp_X]/1 mL
INACTIVE INGREDIENTS: WATER; ALCOHOL

RECAPTURE HGH

ACTIVE INGREDIENT

ACTIVE INGREDIENTS: Human Growth Hormone 30x, IGF-1 30x, Pituitarum 30x, Hepar Suis 6x, Phosphoricum Acidum 3x

PURPOSE

INDICATIONS: Clinical studies suggest the following types of symptom relief associated with aging: Poor muscle/fat balance, low stamina and energy, decrease in sexual function, sleeplessness, weak immune system, irritability, poor memory, dry wrinkled skin.

WARNINGS

WARNING: Keep this and all medicines out of the reach of children. In case of overdose, get medical help or contact a Poison Control Center right away. Do not use if tamper evident seal is broken or missing. If pregnant or nursing, consult a health care professional before use. If new symptoms occur, discontinue use and seek advice of a health care professional.

DOSAGE AND ADMINISTRATION

DIRECTIONS: 2 sprays under the tongue - 3 times a day

INACTIVE INGREDIENTS: 30% Alcohol, Purified Water USP

KEEP OUT OF REACH OF CHILDREN

WARNING: Keep this and all medicines out of the reach of children. In case of overdose, get medical help or contact a Poison Control Center right away.

INDICATIONS AND USAGE

INDICATIONS: Clinical studies suggest the following types of symptom relief associated with aging: Poor muscle/fat balance, low stamina and energy, decrease in sexual function, sleeplessness, weak immune system, irritability, poor memory, dry wrinkled skin.

QUESTIONS

Distributed by
DefyAging.com Inc.
3267 E3300S #302
Salt Lake City, Utah 84109
www.defyaging.com

HOW SUPPLIED

PROPRIETARY DELIVERY SYSTEM

PACKAGE LABEL

RECAPTURE

R

HGH

HOMEOPATHIC

4.0 fl oz (118 ml)